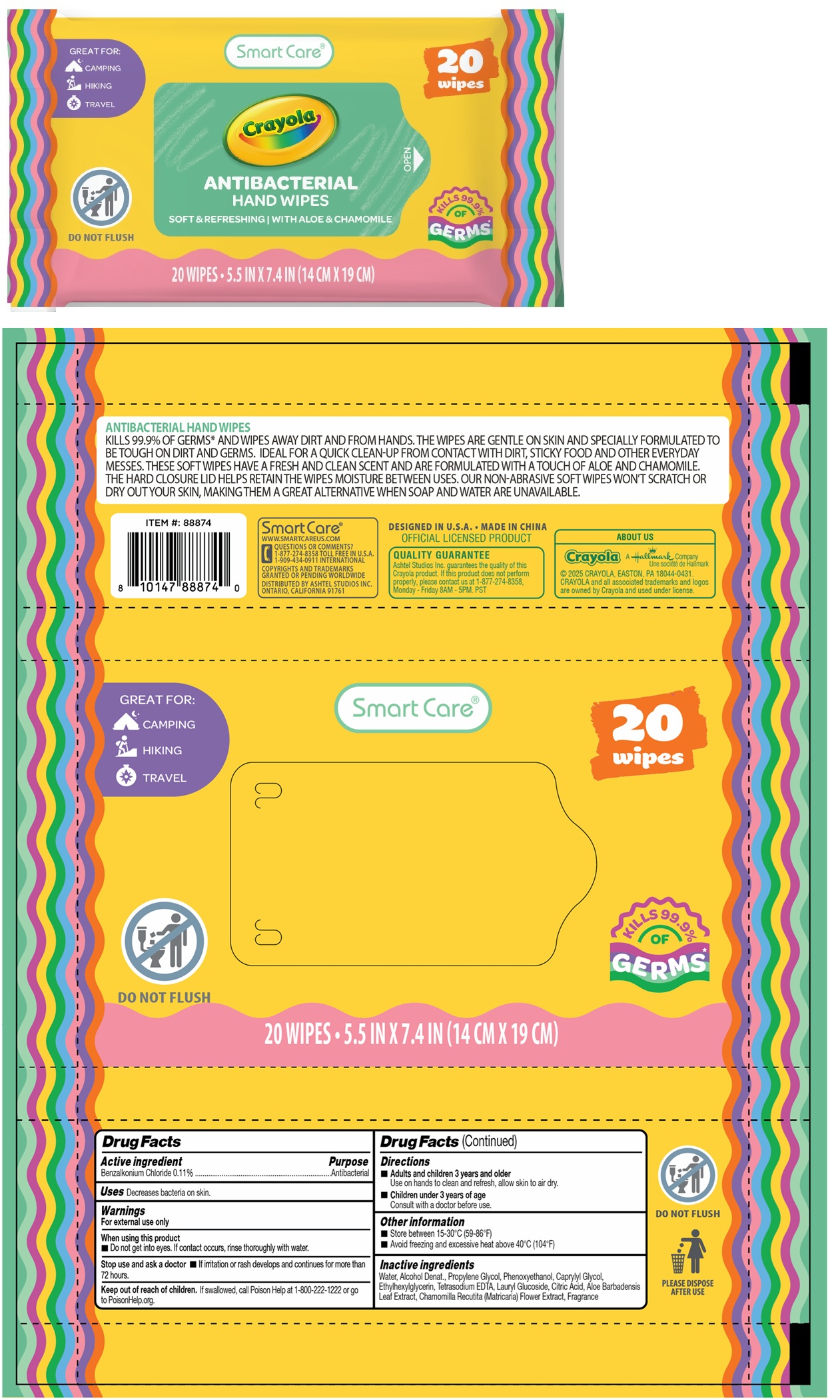 DRUG LABEL: Smart Care Crayola ANTIBACTERIAL HAND WIPES
NDC: 70108-265 | Form: CLOTH
Manufacturer: Ashtel Studios, Inc.
Category: otc | Type: HUMAN OTC DRUG LABEL
Date: 20251111

ACTIVE INGREDIENTS: BENZALKONIUM CHLORIDE 0.11 g/100 mL
INACTIVE INGREDIENTS: WATER; ALCOHOL; PROPYLENE GLYCOL; PHENOXYETHANOL; CAPRYLYL GLYCOL; ETHYLHEXYLGLYCERIN; EDETATE SODIUM; LAURYL GLUCOSIDE; CITRIC ACID MONOHYDRATE; ALOE VERA LEAF; CHAMOMILE

Smart Care® Crayola ANTIBACTERIAL HAND WIPES

Active ingredient

Benzalkonium Chloride 0.11%

Purpose

Antibacterial

Uses

Decreases bacteria on skin.

Warnings

For external use only

When using this product
• Do not get into eyes. If contact occurs, rinse thoroughly with water.

Stop use and ask a doctor • If irritation or rash develops and continues for more than 72 hours.

Keep out of reach of children. If swallowed, call Poison Help at 1-800-222-1222 or go to PoisonHelp.org.

Directions

• Adults and children 3 years and older
Use on hands to clean and refresh, allow skin to air dry.

• Children under 3 years of age
Consult with a doctor before use.

Other information

• Store between 15-30°C (59-86°F)
• Avoid freezing and excessive heat above 40°C (104°F)

Inactive ingredients

Water, Alcohol Denat., Propylene Glycol, Phenoxyethanol, Caprylyl Glycol, Ethylhexylglycerin, Tetrasodium EDTA, Lauryl Glucoside, Citric Acid, Aloe Barbadensis Leaf Extract, Chamomilla Recutita (Matricaria) Flower Extract, Fragrance

GREAT FOR:

CAMPING

HIKING

TRAVEL

SOFT & REFRESHING | WITH ALOE & CHAMOMILE

DO NOT FLUSH

KILLS 99.9% OF GERMS*

PLEASE DISPOSE AFTER USE

KILLS 99.9% OF GERMS* AND WIPES AWAY DIRT AND FROM HANDS. THE WIPES ARE GENTLE ON SKIN AND SPECIALLY FORMULATED TO BE TOUGH ON DIRT AND GERMS. IDEAL FOR A QUICK CLEAN-UP FROM CONTACT WITH DIRT , STICKY FOOD AND OTHER EVERYDAY MESSES. THESE SOFT WIPES HAVE A FRESH AND CLEAN SCENT AND ARE FORMULATED WITH A TOUCH OF ALOE AND CHAMOMILE. THE HARD CLOSURE LID HELPS RETAIN THE WIPES MOISTURE BETWEEN USES. OUR NON- ABRASIVE SOFT WIPES WON'T SCRATCH OR DRY OUT YOUR SKIN, MAKING THEM A GREAT ALTERNATIVE WHEN SOAP AND WATER ARE UNAVAILABLE.

Smart Care®
WWW.SMARTCAREUS.COM

QUESTIONS OR COMMENTS?
1-877-274-8358 TOLL FREE IN U.S.A.
1-909-434-0911 INTERNATIONAL

COPYRIGHTS AND TRADEMARKS GRANTED OR PENDING WORLDWIDE
DISTRIBUTED BY ASHTEL STUDIOS INC.
ONTARIO, CALIFORNIA 91761

DESIGNED IN U.S.A. • MADE IN CHINA

OFFICIAL LICENSED PRODUCT

QUALITY GUARANTEE
Ashtel Studios Inc. guarantees the quality of this Crayola product. If this product does not perform properly, please contact us at 1-877-274-8358, Monday - Friday 8AM- 5PM. PST

ABOUT US

Crayola A Hallmark Company
© 2025 CRAYOLA, EASTON, PA 18044-04331.
CRAYOLA and all associated trademarks and logos are owned by Crayola and used under license.